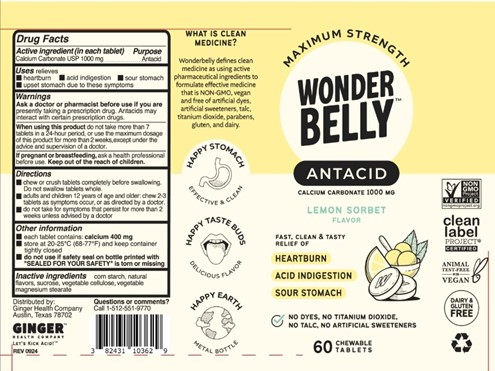 DRUG LABEL: Wonderbelly Maximum Strength Antacid
NDC: 82431-103 | Form: TABLET, CHEWABLE
Manufacturer: Ginger Health Company
Category: otc | Type: HUMAN OTC DRUG LABEL
Date: 20250203

ACTIVE INGREDIENTS: CALCIUM CARBONATE 1000 mg/1 1
INACTIVE INGREDIENTS: MAGNESIUM STEARATE; MICROCRYSTALLINE CELLULOSE; SUCROSE; STARCH, CORN

Lemon Sorbet Antacid

Active ingredient (per tablet)

Calcium Carbonate USP 1000mg

Purpose

Antacid

Uses

relieves

- heartburn
- acid indigestion
- sour stomach
- upset stomach associated with these symptoms

Warnings

Ask a doctor or pharmacists before use if you are presently taking a prescription drug. Antacids

may interact with certain prescription drugs.

When using this product

- do not take more than 7 tablets in 24 hours
- do not use the maximum dosage for more than 2 weeks, except under the advice and supervision of a doctor
- If pregnant or breast-feeding, ask a health professional before use

Keep out of reach of children.

Directions

- adults and children 12 years of age and older; chew 2-3 tablets as symptoms occur, or as directed by a doctor. Chew or crush tablets completely before swallowing.
- for best results, wet in mouth before chewing
- do not take for symptoms that persist for more than 2 weeks unless advised by a doctor

Other Information

- each tablet contains: elemental calcium 400mg
- store at room temperature and keep container tightly closed.

Inactive Ingredients

maize starch, natural flavors, sucrose, vegetable cellulose, vegetable magnesium stearate

Principal Display Panel

Maximum Strength

WONDERBELLY

Antacid

Calcium Carbonate 1000 mg

LEMON SORBET FLAVOR

Fast, Clean & Tasty Relief of

Heartburn

Acid Indigestion

Sour Stomach

No Dyes, No Titanium Dioxide, No Talc, No Artificial Sweeteners

60 Chewable Tablets